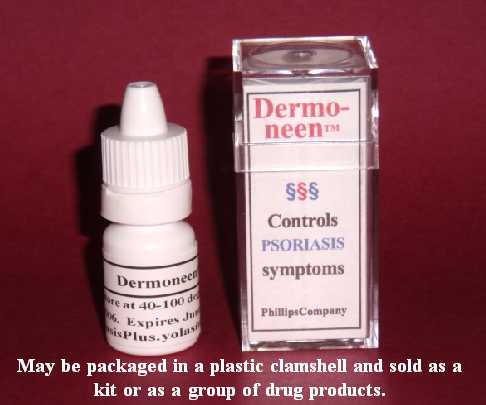 DRUG LABEL: Dermoneen
NDC: 43074-111 | Form: LOTION
Manufacturer: Phillips Company
Category: otc | Type: HUMAN OTC DRUG LABEL
Date: 20110106

ACTIVE INGREDIENTS: SALICYLIC ACID 0.02 mL/1 mL
INACTIVE INGREDIENTS: dimethyl sulfoxide; ascorbic acid; dipropylene glycol; water; sorbic acid; magnesium stearate; stearic acid

DRUG FACTS

DRUG FACTS

Active Ingredient Purpose
Salicylic acid (2%) Psoriasis medication
______________________________________
Uses
n Controls the symptoms of psoriasis.
______________________________________
Warnings
n For external use only
n When using this product, skin irritation and dryness is more likely to occur if you use another topical acne medication at the same time. If irritation occurs, only use one topical acne medication at a time.
n Keep away from children
n Avoid contact with the eyes. If contact occurs, rinse eyes thoroughly with water.
n May be harmful if swallowed or inhaled
______________________________________
Ask a physician
n If symptoms last for more than 7 days or clear up and recur within a few days.
n If the conditions do not improve.
n Before use on children under 2 years.
n Before use if you are allergic to any ingredients listed on this label.
n If condition worsens or does not improve after regular use of this product as directed, consult a physician.
n If condition covers a large area of the body, consult your physician before using this product.
______________________________________
Directions
n Clean the skin thoroughly before applying this product.
n Apply product sparingly to one or two small affected areas during the first 3 days. If no discomfort occurs, follow the directions stated below.
n Apply to affected areas one times daily or as directed by a physician. Each morning, cover the entire affected area with a thin layer of this product. Apply this product by rubbing it in. If any liquid remains on the skin (after a 20-second rub-in), you have applied too much product.
______________________________________
Other information
Store at 40 to 100 degrees F. Net contents: 3 mL. This product contains no alcohol; no animal products.
______________________________________
Inactive ingredients
Water, dimethyl sulfoxide, dipropylene glycol, ascorbic acid, sorbic acid, magnesium stearate, stearic acid.
______________________________________
Questions and Side effects
Use of this product results in no known side effects when used according to directions. Phillips Company, 311 Chickasaw Street, Millerton, OK USA 74750; Tel. 580-746-2430
Email address: hp@valliant.net

ACTIVE INGREDIENTS

Active Ingredient Purpose
Salicylic acid (2%) Psoriasis medication

ASK DOCTOR

Ask a physician
n If symptoms last for more than 7 days or clear up and recur within a few days.
n If the conditions do not improve.
n Before use on children under 2 years.
n Before use if you are allergic to any ingredients listed on this label.
n If condition worsens or does not improve after regular use of this product as directed, consult a physician.
n If condition covers a large area of the body, consult your physician before using this product.

DO NOT USE

n For external use only
n When using this product, skin irritation and dryness is more likely to occur if you use another topical acne medication at the same time. If irritation occurs, only use one topical acne medication at a time.
n Keep away from children
n Avoid contact with the eyes. If contact occurs, rinse eyes thoroughly with water.
n May be harmful if swallowed or inhaled
n If condition worsens or does not improve after regular use of this product as directed, consult a physician.
n If condition covers a large area of the body, consult your physician before using this product.

CHILDREN

Keep away from children
Avoid contact with eyes
May be harmful if swallowed or inhaled

PURPOSE

Active Ingredient Purpose
Salicylic acid (2%) Psoriasis medication

STOP USE

n When using this product, skin irritation and dryness is more likely to occur if you use another topical acne medication at the same time. If irritation occurs, only use one topical acne medication at a time.

WHEN USING

n For external use only
n When using this product, skin irritation and dryness is more likely to occur if you use another topical acne medication at the same time. If irritation occurs, only use one topical acne medication at a time.
n Keep away from children
n Avoid contact with the eyes. If contact occurs, rinse eyes thoroughly with water.
n May be harmful if swallowed or inhaled
n Clean the skin thoroughly before applying this product.
n Apply product sparingly to one or two small affected areas during the first 3 days. If no discomfort occurs, follow the directions stated below.
n Apply to affected areas one times daily or as directed by a physician. Each morning, cover the entire affected area with a thin layer of this product. Apply this product by rubbing it in. If any liquid remains on the skin (after a 20-second rub-in), you have applied too much product.

WARNINGS

n For external use only
n When using this product, skin irritation and dryness is more likely to occur if you use another topical acne medication at the same time. If irritation occurs, only use one topical acne medication at a time.
n Keep away from children
n Avoid contact with the eyes. If contact occurs, rinse eyes thoroughly with water.
n May be harmful if swallowed or inhaled

DOSAGE & ADMINISTRATION

Directions
n Clean the skin thoroughly before applying this product.
n Apply product sparingly to one or two small affected areas during the first 3 days. If no discomfort occurs, follow the directions stated below.
n Apply to affected areas one times daily or as directed by a physician.
n Each morning, cover the entire affected area with a thin layer of this product. Apply this product by rubbing it in. If any liquid remains on the skin (after a 20-second rub-in), you have applied too much product.

USE

Uses
n Controls the symptoms of psoriasis.
Directions
n Clean the skin thoroughly before applying this product.
n Apply product sparingly to one or two small affected areas during the first 3 days. If no discomfort occurs, follow the directions stated below.
n Apply to affected areas one times daily or as directed by a physician.
n Each morning, cover the entire affected area with a thin layer of this product. Apply this product by rubbing it in. If any liquid remains on the skin (after a 20-second rub-in), you have applied too much product.

INACTIVE INGREDIENTS

Water, dimethyl sulfoxide, dipropylene glycol, ascorbic acid, sorbic acid, magnesium stearate, stearic acid.

Image of product